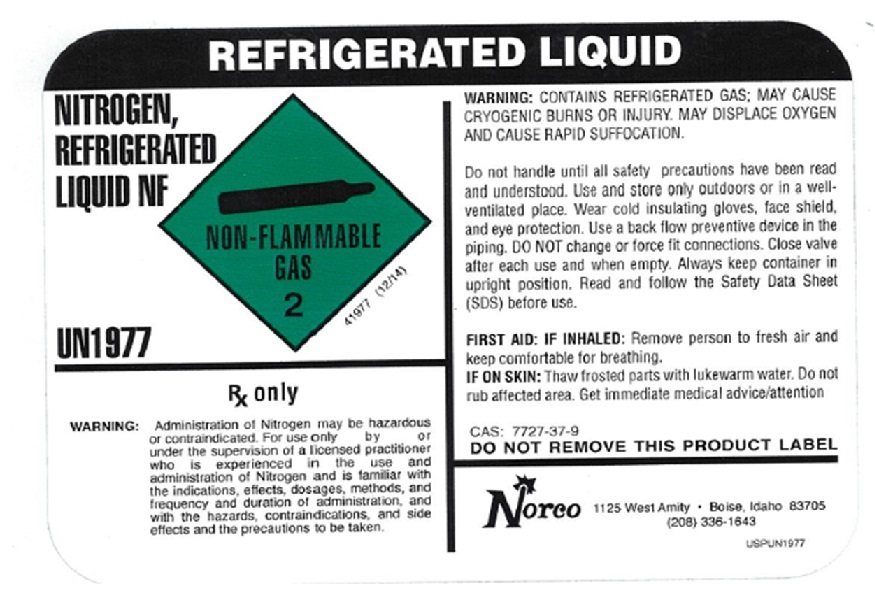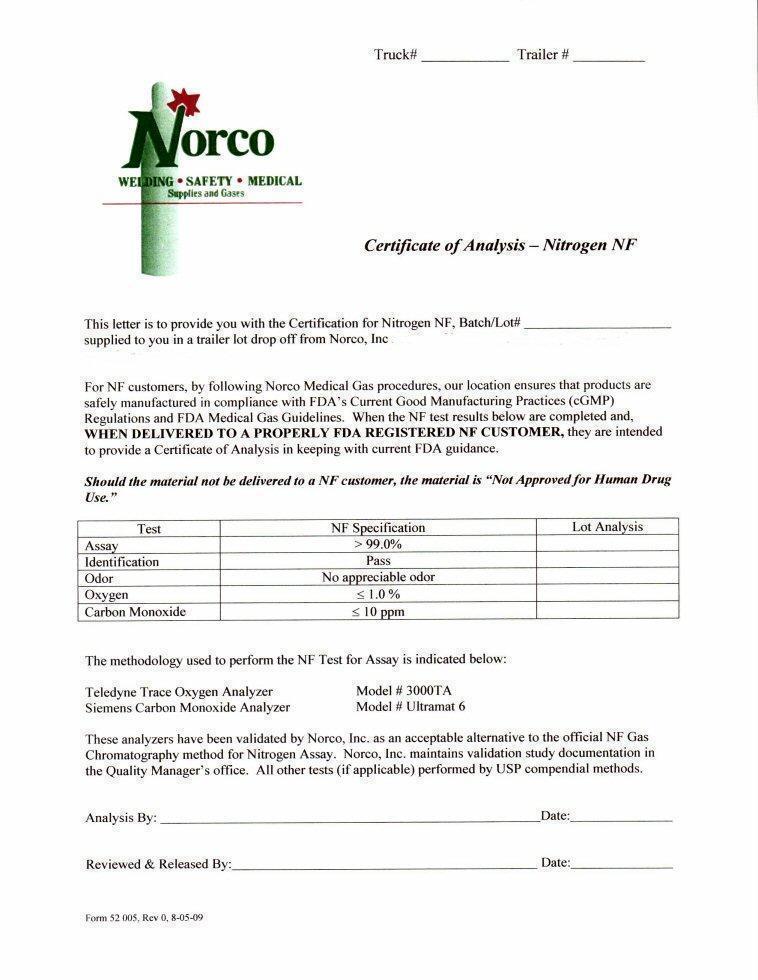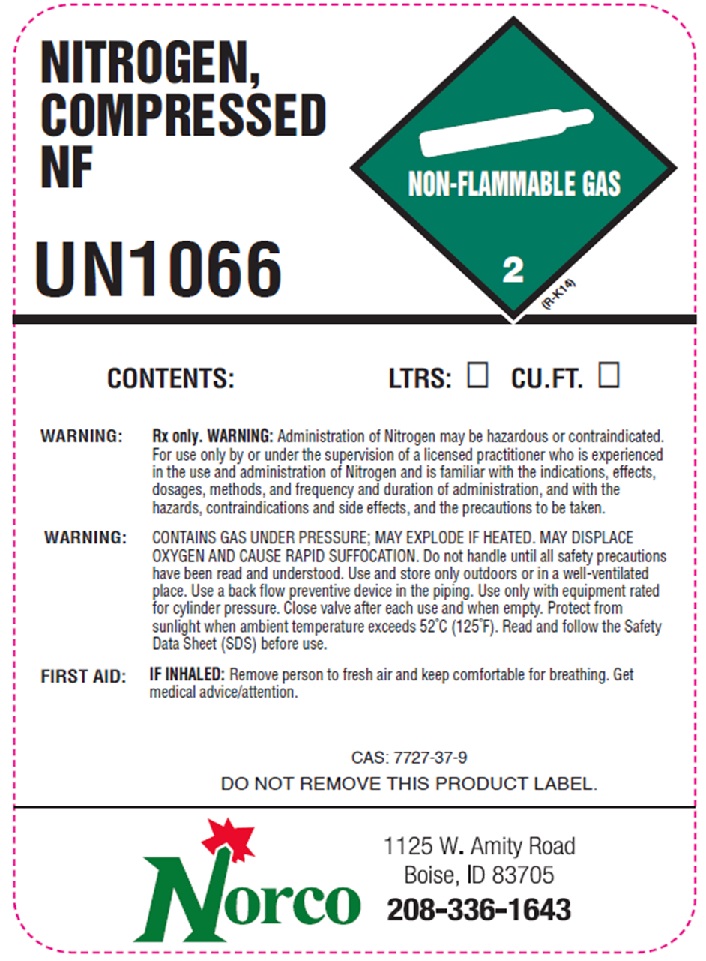 DRUG LABEL: NITROGEN

NDC: 42602-005 | Form: GAS
Manufacturer: Norco, Inc
Category: prescription | Type: HUMAN PRESCRIPTION DRUG LABEL
Date: 20251215

ACTIVE INGREDIENTS: NITROGEN 999 L/1000 L

NITROGEN NF COA

N2 NF CoA

NITROGEN NF LIQUID LABEL

REFRIGERATED LIQUID

NITROGEN, REFRIGERATED

LIQUID NF

NON-FLAMMABLE GAS 2

UN1977

41977 (12/14)

Rx only

WARNING:Administration of Nitrogen may be hazardous
or contraindicated. For use only by or
under the supervision of a licensed practitioner
who is experienced in the use and
administration of Nitrogen and is familiar with
the indications, effects, dosages, methods, and
frequency and duration of administration, and
with the hazards, contraindications, and side
effects and the precautions to be taken.

WARNING:CONTAINS REFRIGERATED GAS: MAY CAUSE
CRYOGENIC BURNS OR INJURY MAYDISPLACE OXYGEN
AND CAUSE RAPID SUFFOCATION.

Do not handle until all safety precautions have been read
and understood. Use and store only outdoors or in a well-
ventilated place. Wear cold insulating gloves. Face shield,
and eye protection. Use a back flow preventive device in the
piping. DO NOT change or force fit connections. Close valve
after each use and when empty. Always keep container in
upright position. Read and follow the Safety Data Sheet
(SDS) before use.

FIRST AID: IF INHALED:Remove person and
keep comfortable for breathing.

IF ON SKIN: Thaw frosted parts with lukewarm water. Do not

rub affected area. Get immediate medical advice/attention.

CAS: 7727-37-9
DO NOT REMOVE THIS PRODUCT LABEL

NORCO1125 W. Amity ● Boise, Idaho 83705
(208) 336-1643

USPUN1977

RES

NITROGEN NF HP LABEL

NITROGEN,

COMPRESSED NF

UN1066 NON-FLAMMABLE GAS 2

(R-K14)
CONTENTS: LTRS: _____ CU. FT. _____

WARNING: Rx only. WARNING:Administration of Nitrogen may be hazardous or contraindicated.
For use only by or under the supervision of a licensed practitioner who is experienced
in the use and administration of Nitrogen and is familiar with the indications, effects,
dosages, methods, and frequency and duration of administration, and with the
hazards, contraindications, and side effects and the precautions to be taken.

WARNING CONTAINS GAS UNDER PRESSURE; MAY EXPLODE IF HEATED. MAY DISPLACE
OXYGEN AND CAUSE RAPID SUFFOCATION. Do not handle until all safety precautions
have been read and understood. Use and store only outdoors or in a well-ventilated
place. Use a back flow preventive device in the piping. Use only with equipment rated
for cylinder pressure. Close valve after each use and when empty. Protect from
sunlight when ambient temperature exceeds 52 C (125 F). Read and follow the Safety
Data Sheet (SDS) before use.

FIRST AID: IF INHALED:Remove person and keep comfortable for breathing. Get
Medical/advice/attention.

CAS: 7727-37-9
DO NOT REMOVE THIS PRODUCT LABEL

NORCO 1125 W. Amity Rd.

Boise, Idaho 83705

(208) 336-1643

res